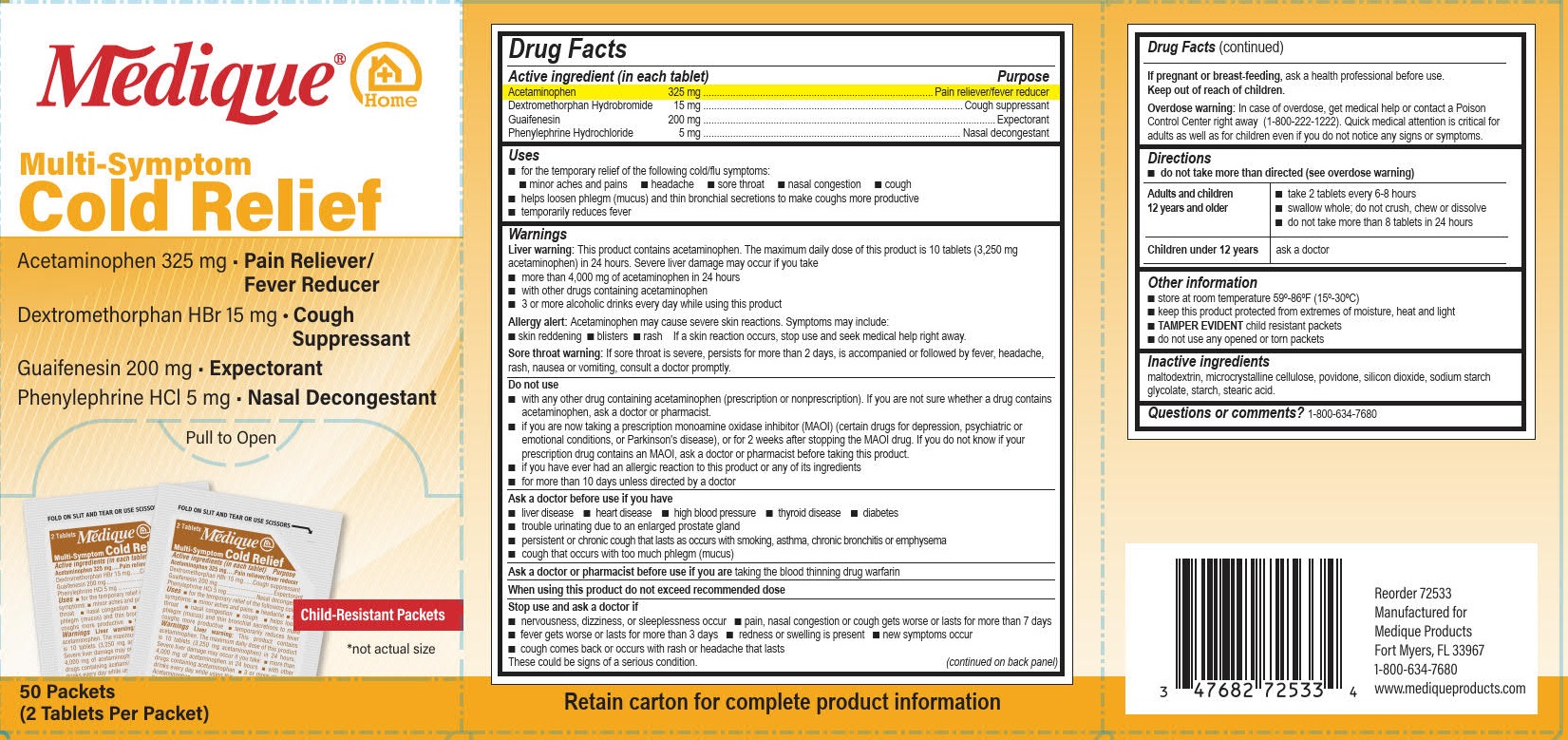 DRUG LABEL: Medique at Home Cold Relief
NDC: 47682-725 | Form: TABLET
Manufacturer: Unifirst First Aid Corporation
Category: otc | Type: HUMAN OTC DRUG LABEL
Date: 20220317

ACTIVE INGREDIENTS: DEXTROMETHORPHAN HYDROBROMIDE 15 mg/1 1; GUAIFENESIN 200 mg/1 1; PHENYLEPHRINE HYDROCHLORIDE 5 mg/1 1; ACETAMINOPHEN 325 mg/1 1
INACTIVE INGREDIENTS: STARCH, CORN; STEARIC ACID; CELLULOSE, MICROCRYSTALLINE; SILICON DIOXIDE; MALTODEXTRIN; POVIDONE, UNSPECIFIED; SODIUM STARCH GLYCOLATE TYPE A CORN

Medique @ Home Cold Relief

Drug Facts

Active ingredients (in each tablet)

Acetaminophen 325 mg

Dextromethorphan Hydrobromide 15 mg

Guaifenesin 200 mg

Phenylephrine Hydrochloride 5 mg .

Purpose

Pain reliever/ fever reducer

Cough suppressant

Expectorant

Nasal decongestant

Uses

■ for the temporary relief of the following cold/flu symptoms:

■ minor aches and pains ■ headache ■ sore throat ■ nasal congestion ■ cough

■ helps loosen phlegm (mucus) and thin bronchial secretions to make coughs more productive

■ temporarily reduces fever

Warnings

Liver warning: This product contains acetaminophen. The maximum daily dose of this product is 10 tablets (3,250 mg acetaminophen) in 24 hours. Severe liver damage may occur if you take

■ more than 4,000 mg of acetaminophen in 24 hours

■ with other drugs containing acetaminophen

■ 3 or more alcoholic drinks every day while using this product

Allergy alert: Acetaminophen may cause severe skin reactions. Symptoms may include:

■ skin reddening

■ blisters

■ rash

If a skin reaction occurs, stop use and seek medical help right away.

Sore throat warning: If sore throat is severe, persists for more than 2 days, is accompanied or followed by fever, headache, rash, nausea or vomiting, consult a doctor promptly.

Do not use

■ with any other drug containing acetaminophen (prescription or nonprescription). If you are not sure whether a
drug contains acetaminophen, ask a doctor or pharmacist.

■ if you are now taking a prescription monoamine oxidase inhibitor (MAOI) (certain drugs for depression,
psychiatric or emotional conditions, or Parkinson's disease), or for 2 weeks after stopping the MAOI drug. If
you do not know if your prescription drug contains an MAOI, ask a doctor or pharmacist before taking this
product.

■ if you have ever had an allergic reaction to this product or any of its ingredients

■ for more than 10 days unless directed by a doctor

Ask a doctor before use if you have

■ liver disease

■ heart disease

■ high blood pressure

■ thyroid disease

■ diabetes

■ trouble urinating due to an enlarged prostate gland

■ persistent or chronic cough that lasts as occurs with smoking, asthma, chronic bronchitis or emphysema

■ cough that occurs with too much phlegm (mucus)

Ask a doctor or pharmacist before use if you are taking the blood thinning drug warfarin

When using this product do not exceed recommended dose

Stop use and ask a doctor if

■ nervousness, dizziness, or sleeplessness occur

■ pain, nasal congestion or cough gets worse or lasts for more than 7 days

■ fever gets worse or lasts for more than 3 days

■ redness or swelling is present

■ new symptoms occur

■ cough comes back or occurs with rash or headache that lasts

These could be signs of a serious condition.

PREGNANCY OR BREAST FEEDING

If pregnant or breast-feeding, ask a health professional before use.

Keep out of reach of children.

Overdose warning

In case of overdose, get medical help or contact a Poison Control Center right away (1-800-222-1222). Quick medical attention is critical for adults as well as for children even if you do not notice any signs or symptoms.

Directions

■ do not take more than directed (see overdose warning)

Adults and children12 years and older

■ take 2 tablets every 6-8 hours

■ swallow whole; do not crush, chew or dissolve

■ do not take more than 8 tablets in 24 hours

Children under 12 years

ask a doctor

Other information

■ store at room temperature 68º-77ºF (20º-25ºC)

■ keep this product protected from extremes of moisture, heat and light

■ Tamper Evident child resistant packets

■ do not use any opened or torn packets

Inactive ingredients

maltodextrin, microcrystalline cellulose, povidone, silicon dioxide, sodium starch glycolate, starch, stearic acid

Questions or comments? 1-800-634-7680

PACKAGE LABEL

Medique® @ Home

Multi-Symptom Cold Relief

Acetaminophen 325 mg • Pain Reliever/ Fever Reducer

Dextromethorphan Hydrobromide 15 mg • Cough Suppressant

Guaifenesin 200 mg • Expectorant

Phenylephrine Hydrochloride 5 mg • Nasal Decongestant

Pull to Open

Child-Resistant Packets

*not actual size

50 Packets

(2 Tablets Per Packet)